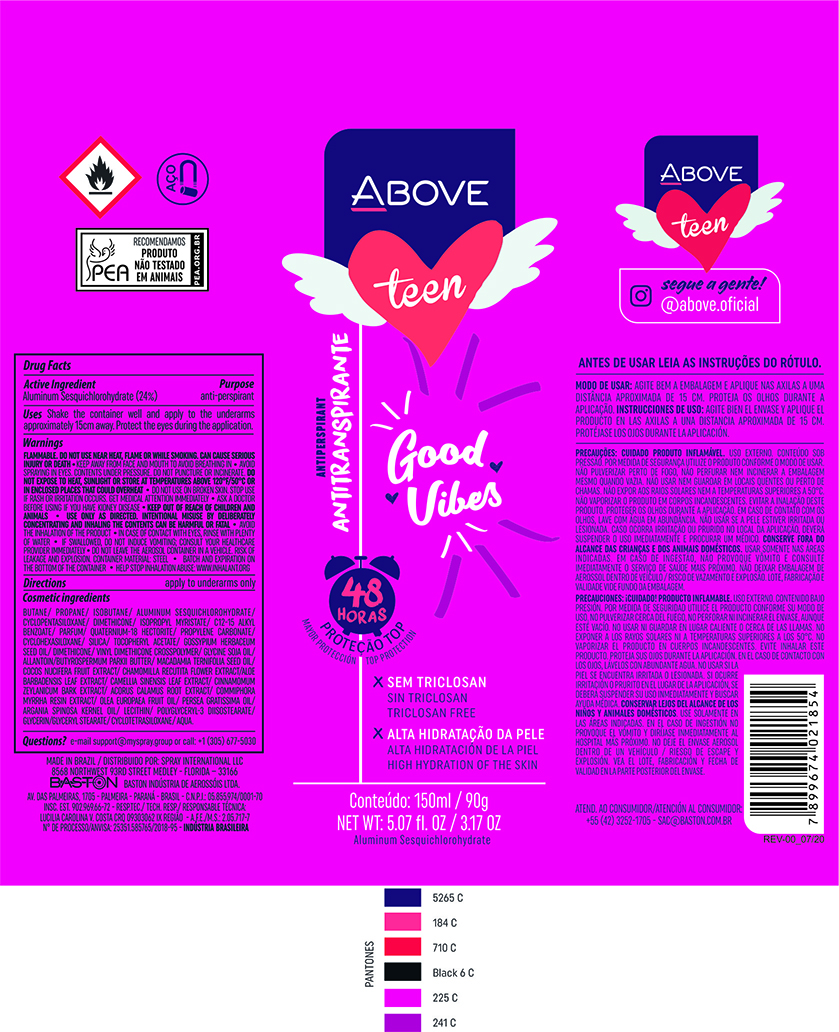 DRUG LABEL: Antiperspirant Above Teen Good Vibes
NDC: 73306-1111 | Form: AEROSOL, SPRAY
Manufacturer: Baston Industria de Aerossóis Ltda
Category: otc | Type: HUMAN OTC DRUG LABEL
Date: 20241226

ACTIVE INGREDIENTS: ALUMINUM SESQUICHLOROHYDRATE 24 g/100 g
INACTIVE INGREDIENTS: ALOE VERA LEAF; DIMETHICONE; GLYCERIN; GREEN TEA LEAF; CINNAMON BARK OIL; LEVANT COTTON SEED; POLYGLYCERYL-3 DIISOSTEARATE; SILICA DIMETHYL SILYLATE; ACORUS CALAMUS ROOT; VINYL DIMETHICONE/METHICONE SILSESQUIOXANE CROSSPOLYMER; WATER; AVOCADO OIL; SHEA BUTTER; MACADAMIA OIL; CYCLOMETHICONE 5; MYRRH OIL; ISOPROPYL MYRISTATE; LECITHIN, SOYBEAN; COCONUT; ALLANTOIN; BUTANE; PROPANE; ARGAN OIL; GLYCERYL MONOSTEARATE; CHAMOMILE; ISOBUTANE; .ALPHA.-TOCOPHEROL ACETATE; DISTEARDIMONIUM HECTORITE; PROPYLENE CARBONATE

Antiperspirant Above Teen Good Vibes Aerosol